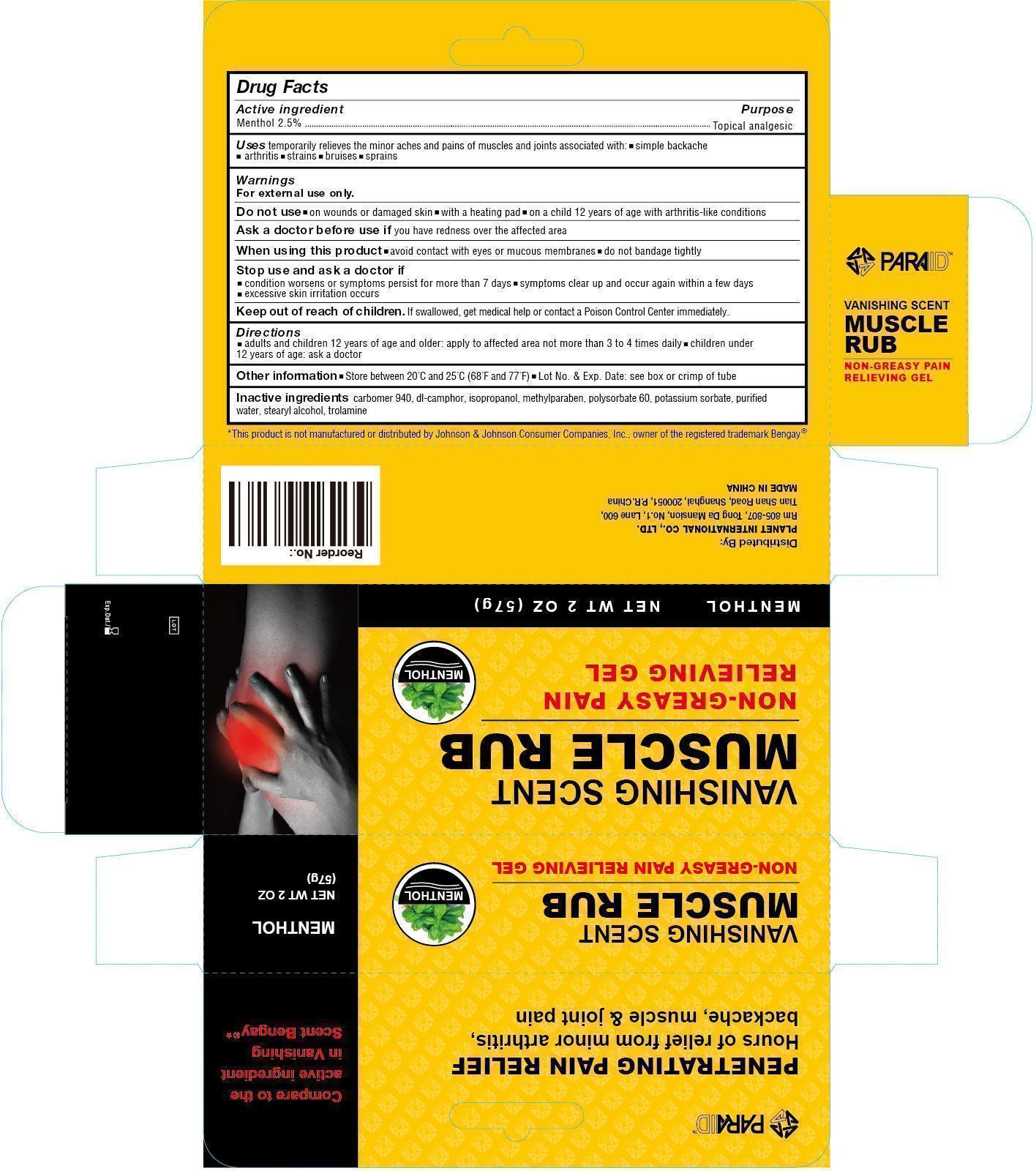 DRUG LABEL: Vanishing Scent Muscle Rub Gel
NDC: 52486-012 | Form: GEL
Manufacturer: McCure Health Solutions Inc.
Category: otc | Type: HUMAN OTC DRUG LABEL
Date: 20161228

ACTIVE INGREDIENTS: MENTHOL 25 mg/1 g
INACTIVE INGREDIENTS: CARBOMER 940; CAMPHOR (SYNTHETIC); ISOPROPYL ALCOHOL; METHYLPARABEN; POLYSORBATE 60; POTASSIUM SORBATE; WATER; STEARYL ALCOHOL; TROLAMINE

Vanishing Scent Muscle Rub Gel

Active ingredient

Menthol 2.5%

Purpose

Topical analgesic

Uses

temporarily relieves the minor aches and pains of muscles and joints associated with: • simple backache • arthritis • strains • bruises • sprains

Warnings

For external use only.

Do not use

• on wounds or damaged skin • with a heating pad • on a child 12 years of age with arthritis-like conditions

Ask a doctor before use if

you have redness over the affected area

When using this product

• avoid contact with eyes or mucous membranes • do not bandage tightly

Stop use and ask a doctor if

• condition worsens or symptoms persist for more than 7 days • symptoms clear up and occur again within a few days • excessive skin irritation occurs

Keep out of reach of children.

If swallowed, get medical help or contact a Poison Control Center immediately.

Directions

• adults and children 12 years of age and older: apply to affected area not more than 3 to 4 times daily • children under 12 years of age: ask a doctor

Other information

• Store between 20 C and 25 C (68 F and 77 F) • Lot No. & Exp. Date. see box or crimp of tube

Inactive ingredients

CARBOMER 940, DL-CAMPHOR, ISOPROPANOL, METHYLPARABEN, POLYSORBATE 60, POTASSIUM SORBATE, PURIFIED WATER, STEARYL ALCOHOL, TROLAMINE